DRUG LABEL: Oxygen
NDC: 59863-325 | Form: GAS
Manufacturer: Banner Home Care of Arizona 
Category: prescription | Type: HUMAN PRESCRIPTION DRUG LABEL
Date: 20091117

ACTIVE INGREDIENTS: Oxygen 99 L/100 L

Oxygen